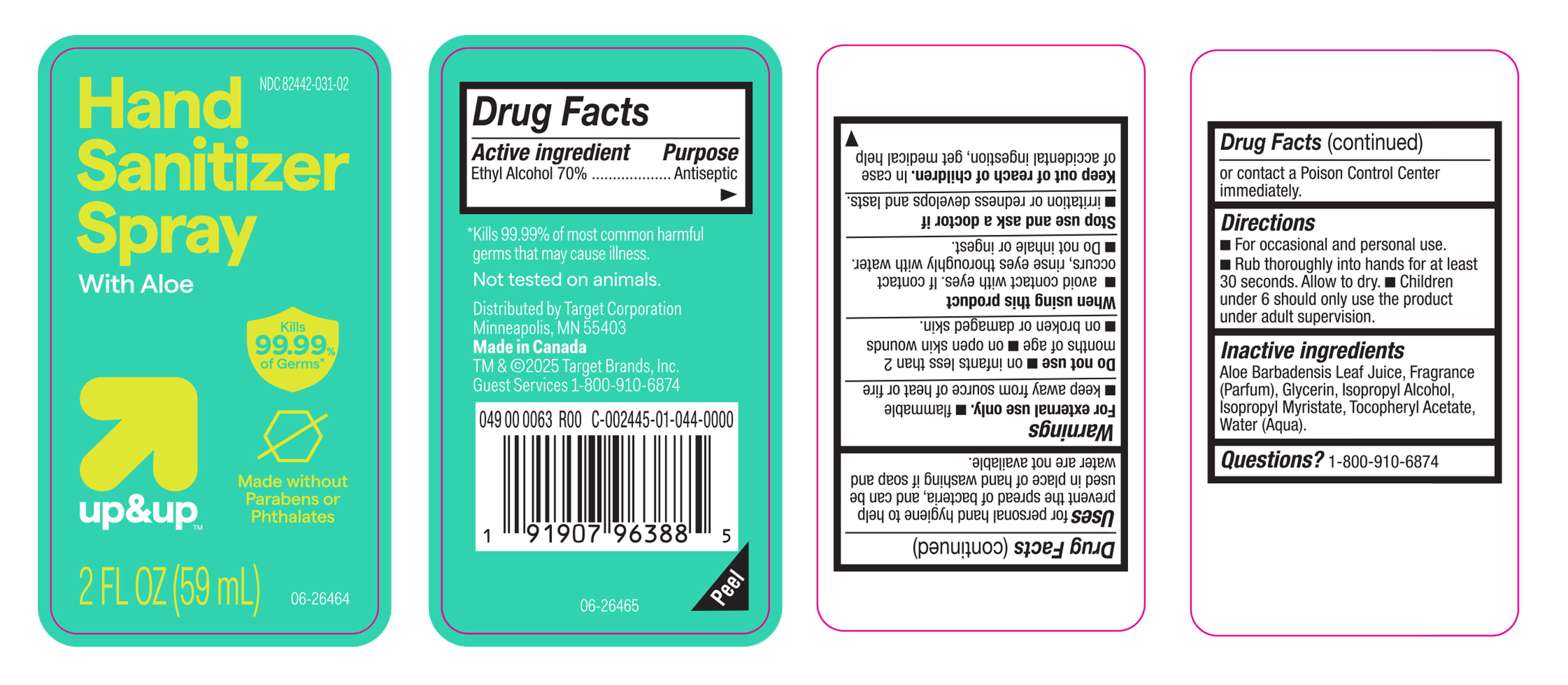 DRUG LABEL: Ethanol
NDC: 82442-031 | Form: GEL
Manufacturer: TARGET CORPORATION INC.
Category: otc | Type: HUMAN OTC DRUG LABEL
Date: 20250320

ACTIVE INGREDIENTS: ALCOHOL 70 mL/100 mL
INACTIVE INGREDIENTS: ISOPROPYL MYRISTATE; ISOPROPYL ALCOHOL; GLYCERIN; .ALPHA.-TOCOPHEROL ACETATE, D-; WATER; ALOE BARBADENSIS LEAF JUICE; FRAGRANCE CLEAN ORC0600327

Target Hand Sanitizer Clear Gel with Aloe, NDC-82442-031

Active Ingredient

Ethyl Alcohol 70%

Purpose

Antiseptic

Uses

For personal hand hygiene to help prevent the spread of bacteria, and can be used in place of hand washing if soap and water are not available.

Warnings

For External use only.

- Flammable.
- Keep away from source of heat or fire.

When using this product

- Avoid contact with eyes. If contact occurs, rinse eyes thoroughly with water.
- Do not inhale or ingest.

Stop use and ask a doctor if

- irritation or redness develops and lasts.

Keep out of reach of children

In case of accidental ingestion, get medical help or contact a Poison Control Center immediately.

Directions

- For occassional and personal use.
- Rub thoroughly into hands for at least 30 seconds. Allow to dry.
- Children under 6 should only use the product under adult supervision.

Inactive Ingredients

Aloe Barbadensis Leaf Juice, Fragrance (Parfum), Glycerin, Isopropyl Alcohol, Isopropyl Myristate, Tocopheryl Acetate, Water (Aqua).

Questions?

1-800-910-6874.